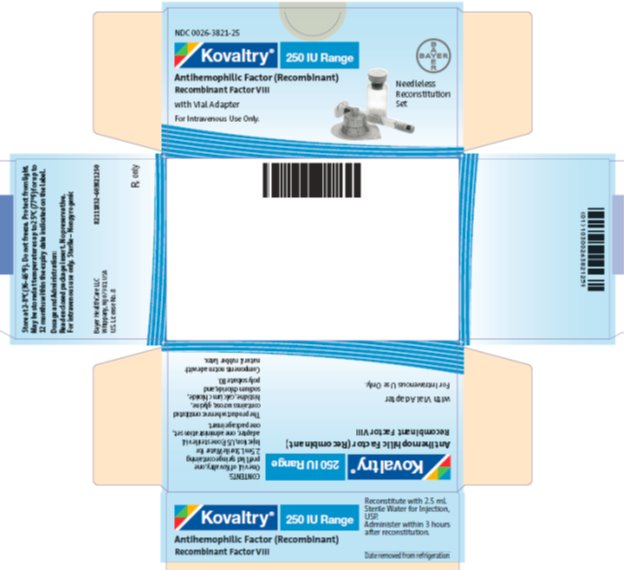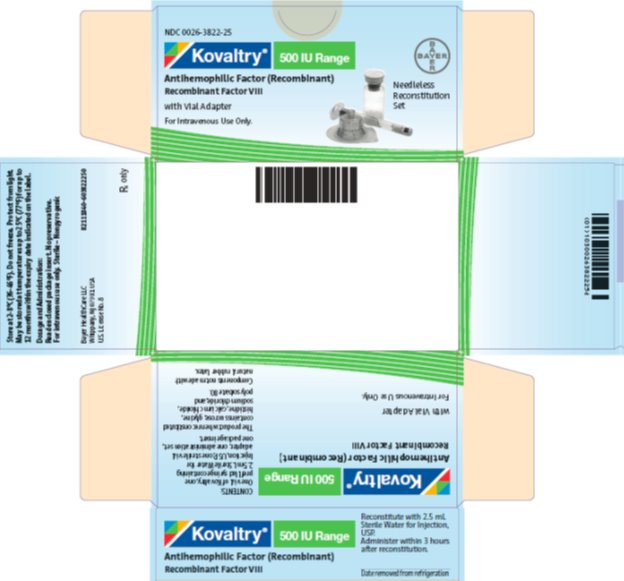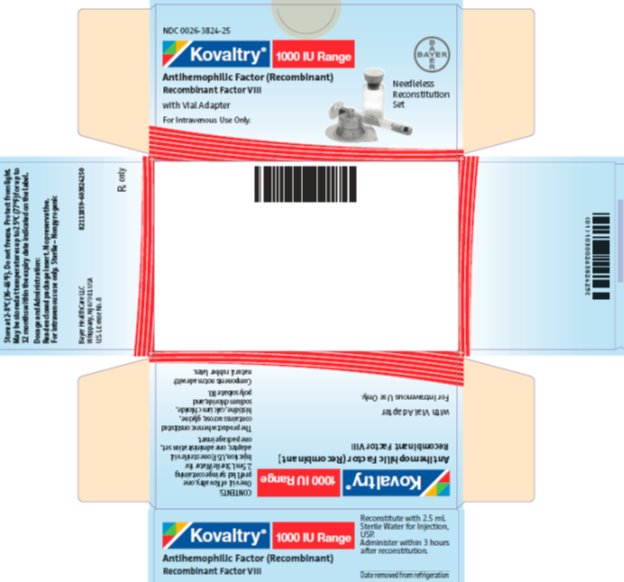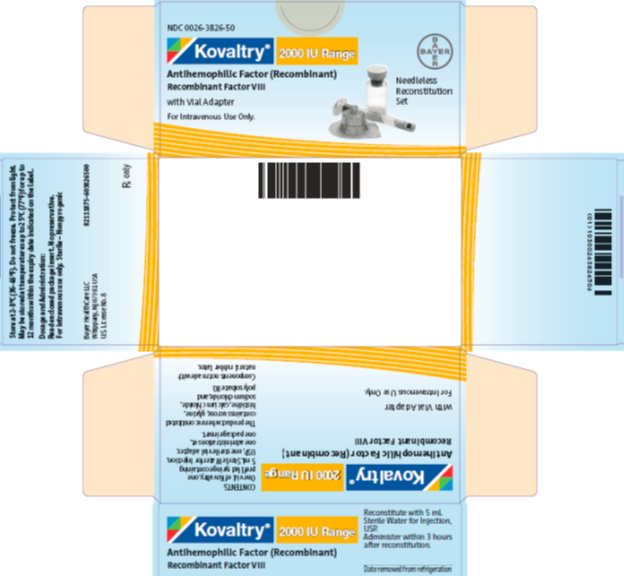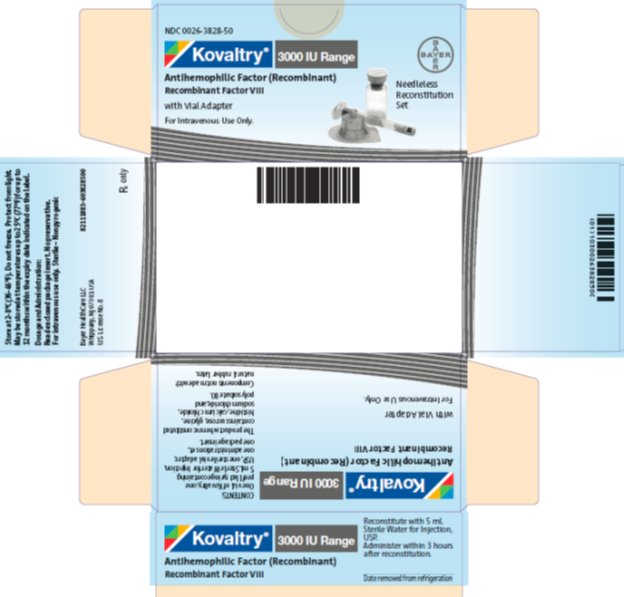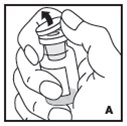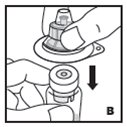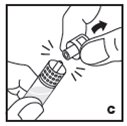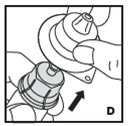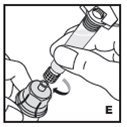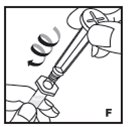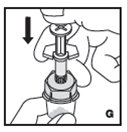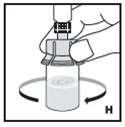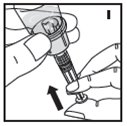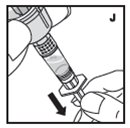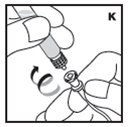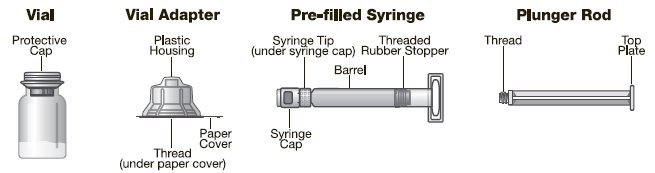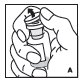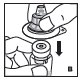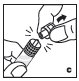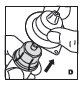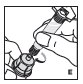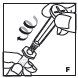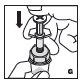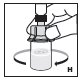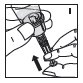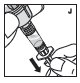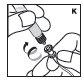 DRUG LABEL: Kovaltry
NDC: 0026-3821 | Form: KIT | Route: INTRAVENOUS
Manufacturer: Bayer HealthCare LLC
Category: other | Type: PLASMA DERIVATIVE
Date: 20221201

ACTIVE INGREDIENTS: ANTIHEMOPHILIC FACTOR, HUMAN RECOMBINANT 250 [iU]/2.5 mL
INACTIVE INGREDIENTS: CALCIUM CHLORIDE; SODIUM CHLORIDE; GLYCINE; HISTIDINE; POLYSORBATE 80; SUCROSE; WATER

HIGHLIGHTS OF PRESCRIBING INFORMATION

These highlights do not include all the information needed to use KOVALTRY safely and effectively. See full prescribing information for KOVALTRY.
KOVALTRY [Antihemophilic Factor (Recombinant)]
Lyophilized Powder for Solution for Intravenous Injection – Reconstitution with Vial Adapter
Initial U.S. Approval: 2016

1 INDICATIONS AND USAGE

KOVALTRY®, Antihemophilic Factor (Recombinant), is a recombinant, human DNA sequence derived, full length Factor VIII concentrate indicated for use in adults and children with hemophilia A (congenital Factor VIII deficiency) for:

• On-demand treatment and control of bleeding episodes

• Perioperative management of bleeding

• Routine prophylaxis to reduce the frequency of bleeding episodes

KOVALTRY is not indicated for the treatment of von Willebrand disease (1).

2 DOSAGE AND ADMINISTRATION

For intravenous use after reconstitution only.

Control of bleeding episodes and perioperative management (2.1)

- Required dose (IU) = body weight (kg) x desired Factor VIII rise (% of normal or IU/dL) x reciprocal of expected/observed recovery (e.g., 0.5 for a recovery of 2 IU/dL per IU/kg).
- Estimated Increment of Factor VIII (IU/dL or % of normal) = [Total Dose (IU)/body weight (kg)] x 2 (IU/dL per IU/kg).

Routine prophylaxis (2.1)

- Adults and adolescents: 20-40 IU/kg 2 or 3 times per week.
- Children ≤12 years old: 25-50 IU/kg 2 times per week, 3 times per week or every other day.

3 DOSAGE FORMS AND STRENGTHS

KOVALTRY is available as lyophilized powder in single-dose vials containing nominally 250, 500, 1000, 2000, or 3000 IU. Each vial of KOVALTRY contains the labeled amount of recombinant Factor VIII in IU (3).

4 CONTRAINDICATIONS

Do not use in patients who have history of hypersensitivity reactions to the active substance, mouse or hamster protein, or other constituents of the product (4).

5 WARNINGS AND PRECAUTIONS

- Hypersensitivity reactions, including anaphylaxis, are possible. Should symptoms occur, discontinue treatment with KOVALTRY and administer appropriate treatment (5.1).
- Development of Factor VIII neutralizing antibodies has occurred. Perform an assay that measures Factor VIII inhibitor concentration if expected plasma Factor VIII activity levels are not attained, or if bleeding is not controlled as expected with administered dose (5.2, 5.5).

6 ADVERSE REACTIONS

The most frequently reported adverse reactions in clinical trials (≥5%) were inhibitors in previously untreated patients (PUPs)/minimally treated patients (MTPs), pyrexia, headache, and rash (6).

To report SUSPECTED ADVERSE REACTIONS, contact Bayer HealthCare at 1-888-842-2937 or FDA at 1-800-FDA-1088 or www.fda.gov/medwatch.

8 USE IN SPECIFIC POPULATIONS

Pediatric Use: Due to higher clearance (body weight adjusted) in children ≤12 years of age, higher or more frequent dosing may be needed (8.4).

FULL PRESCRIBING INFORMATION

1 INDICATIONS AND USAGE

KOVALTRY, Antihemophilic Factor (Recombinant), is a recombinant, human DNA sequence derived, full length Factor VIII concentrate indicated for use in adults and children with hemophilia A (congenital Factor VIII deficiency) for:

- On-demand treatment and control of bleeding episodes
- Perioperative management of bleeding
- Routine prophylaxis to reduce the frequency of bleeding episodes

KOVALTRY is not indicated for the treatment of von Willebrand disease.

2 DOSAGE AND ADMINISTRATION

For intravenous use after reconstitution only.

2.1 Dose

- Dosage and duration of treatment depend on the severity of the Factor VIII deficiency, the location and extent of bleeding, and the patient’s clinical condition. Careful control of replacement therapy is especially important in cases of major surgery or life-threatening bleeding episodes.
- Each vial label of KOVALTRY states the Factor VIII potency in international units (IU). One IU is defined by the current WHO (World Health Organization) international standard (IS) for Factor VIII concentrate.
- Potency assignment for KOVALTRY is determined using a chromogenic substrate assay. A field study involving 41 clinical laboratories from around the world measured recoveries of KOVALTRY spiked into hemophilic plasma. The results of the field study indicated that the Factor VIII activity of KOVALTRY can be accurately measured in plasma using either a one-stage clotting or chromogenic substrate assay according to routine methods of the testing laboratory.
- The required dose for a desired Factor VIII level expressed as IU/dL (or % of normal) can be estimated using the following formula:
Required dose (IU) = body weight (kg) x desired Factor VIII rise (% of normal or IU/dL)
  x reciprocal of expected/observed recovery (e.g., 0.5 for a recovery of 2 IU/dL per IU/kg)
The expected in vivo peak increase of Factor VIII level expressed as IU/dL (or % of normal) can be estimated using the following formula:
Estimated increment of Factor VIII (IU/dL or % of normal) = [Total dose (IU)/body weight (kg)]
  x 2 (IU/dL per IU/kg)
Examples (assuming patient’s baseline Factor VIII is <1%):
- A peak of 50% [50 IU/dL] is required in a 20 kg child. In this situation, the required dose of KOVALTRY would be 20 kg x 50 IU/dL x 0.5 (for recovery of 2 IU/dL per IU/kg) = 500 IU
- A dose of 2000 IU of KOVALTRY administered to a 50 kg patient should be expected to result in post-infusion Factor VIII increase of 2000 IU / 50 kg (body weight) x 2 IU/dL per IU/kg = 80 IU/dL (80% of normal)
- Adjust dose to the patient’s clinical response. Patients may vary in their pharmacokinetic (e.g., half-life, incremental recovery) and clinical responses to KOVALTRY.
- On-demand Treatment and Control of Bleeding Episodes

A guide for dosing KOVALTRY for the on-demand treatment and control of bleeding episodes is provided in Table 1. The goal of treatment is to maintain a plasma Factor VIII activity level at or above the plasma levels (in % of normal or in IU/dL) outlined in Table 1.

Table 1: Dosing for Control of Bleeding Episodes
Degree of Bleeding | Factor VIII Level Required (IU/dL or % of normal) | Frequency of Doses (hours) | Duration of Therapy (days)
Minor (Early hemarthrosis, minor muscle, oral bleeds) | 20–40 | Repeat every 12–24 hours | At least 1 day, until bleeding episode as indicated by pain is resolved or healing is achieved
Moderate (More extensive hemarthrosis, muscle bleeding, or hematoma) | 30–60 | Repeat every 12–24 hours | 3 to 4 days or more until pain and acute disability are resolved
Major (intracranial, intra-abdominal or intrathoracic hemorrhages, gastrointestinal bleeding, central nervous system bleeding, bleeding in the retropharyngeal or retroperitoneal spaces, or iliopsoas sheath, life or limb threatening hemorrhage) | 60–100 | Repeat every 8–24 hours | Until bleeding is resolved

Perioperative Management of Bleeding

A guide for dosing KOVALTRY during surgery (perioperative management) is provided in Table 2. The goal of treatment is to maintain a plasma Factor VIII activity level at or above the plasma level (in % of normal or in IU/dL) outlined in Table 2. During major surgery, monitoring with appropriate laboratory tests, including serial Factor VIII activity assays, is highly recommended [see Warnings and Precautions (5.5)].

Table 2: Dosing for Perioperative Management
Type of Surgery | Factor VIII Level Required (IU/dL or % of normal) | Frequency of Doses (hours) | Duration of Therapy (days)
Minor (Such as tooth extraction) | 30–60 (pre- and post-operative) | Repeat every 24 hours | At least 1 day until healing is achieved
Major (Such as intracranial, intra-abdominal, intrathoracic, or joint replacement surgery) | 80–100 (pre- and post-operative) | Repeat every 8–24 hours | Until adequate wound healing is complete, then continue therapy for at least another 7 days to maintain Factor VIII activity of 30–60% (IU/dL)

Routine Prophylaxis

- Individualize the patient’s dose based on clinical response.
- Adults and adolescents: 20 to 40 IU of KOVALTRY per kg of body weight two or three times per week.
- Children ≤12 years old: 25 to 50 IU of KOVALTRY per kg body weight twice weekly, three times weekly, or every other day according to individual requirements [see Use in Specific Populations (8.4)].

2.2 Preparation and Reconstitution

- Reconstitute and administer KOVALTRY with the components provided with each package. If any component of the package is opened or damaged, do not use this component.

The procedures below are provided as general guidelines for the reconstitution of KOVALTRY using the sterile vial adapter with a 15 micrometer filter and a prefilled diluent syringe, which together serve as an alternative needleless reconstitution system.

Usability Testing of Vial Adapter

Usability testing was conducted with 60 users, including 15 pediatric hemophilia A patients (between 10-17 years of age), 15 adult hemophilia A patients (≥18 years of age), 15 caregivers, and 15 healthcare providers. To mimic real life, the pediatric and adult patients and the caregivers were given minimal training, which included participants performing a supervised reconstitution and later performing a single unaided reconstitution. Healthcare providers were untrained in this study and could learn the procedure from the provided Instructions for Use. All participants were able to successfully and safely use the vial adapter device for reconstitution.

Reconstitution

- Work on a clean surface and wash hands thoroughly using soap and warm water before performing the procedures.
- Reconstitute KOVALTRY with the components provided with each package. If any component of the package is opened or damaged, do not use this component.
- Filter the reconstituted product to remove potential particulate matter in the solution. Filtering is achieved by using the vial adapter.

1. Warm both unopened KOVALTRY vial and prefilled diluent syringe in your hands to a comfortable temperature (do not exceed 37°C or 99°F).

2. Remove the protective cap from the vial (A). Aseptically cleanse the rubber stopper with a sterile alcohol swab, being careful not to handle the rubber stopper.

3. Place the product vial on a firm, non-skid surface. Peel off the paper cover on the vial adapter plastic housing. Do not remove the adapter from the plastic housing. Holding the adapter housing, place over the product vial and firmly press down (B). The adapter will snap over the vial cap. Do not remove the adapter housing at this step.

4. Holding the syringe by the barrel, snap the syringe cap off the tip (C). Do not touch the syringe tip with your hand or any surface. Set the syringe aside for further use.

5. Now remove and discard the adapter plastic housing (D).

6. Attach the prefilled syringe to the vial adapter thread by turning clockwise (E).

7. Remove the clear plastic plunger rod from the carton. Grasp the plunger rod by the top plate. Avoid touching the sides and threads of the plunger rod. Attach the plunger rod by turning it clockwise into the threaded rubber stopper of the prefilled syringe (F).

8. Inject the diluent slowly by pushing down on the plunger rod (G).

9. Swirl vial gently until all powder on all sides of the vial is dissolved (H). Do not shake vial. Be sure that all powder is completely dissolved. Do not use if solution contains visible particles or is cloudy.

10. Push down on the plunger to push all air back into the vial. Then while holding the plunger down, turn the vial with syringe upside-down (invert) so the vial is now above the syringe (I).

11. Withdraw all the solution into the syringe by pulling the plunger rod back slowly and smoothly (J). Tilt the vial to the side and back to make sure all the solution has been drawn toward the large opening in the rubber stopper and into the syringe. Remove as much air as possible before removing the syringe from the vial by slowly and carefully pushing the air back into the vial.

12. Detach the syringe with plunger rod from the vial adapter by turning counter-clockwise. Attach the syringe to the administration set provided and inject intravenously (K).
Note: follow instructions for infusion set provided.

Pooling

If the dose requires more than one vial, reconstitute each vial as described above with the diluent syringe provided. Use a larger plastic syringe (not provided) to combine the content of the vials into the syringe.

2.3 Administration

For intravenous use only.

- Inspect reconstituted KOVALTRY visually for particulate matter and discoloration prior to administration. Do not use if you notice any particulate matter or discoloration.
- Administer reconstituted KOVALTRY as soon as possible. If not, store at room temperature for no longer than 3 hours.
- Infuse KOVALTRY intravenously over a period of 1 to 15 minutes. Adapt the rate of administration to the response of each individual patient.

3 DOSAGE FORMS AND STRENGTHS

KOVALTRY is available as a lyophilized powder in single-dose glass vials containing nominally 250, 500, 1000, 2000, or 3000 IU of recombinant Factor VIII per vial.

Each vial of KOVALTRY is labeled with actual Factor VIII potency expressed in IU determined using a chromogenic substrate assay. This potency assignment employs a Factor VIII concentrate standard that is referenced to the current WHO International Standard for Factor VIII concentrate, and is evaluated by appropriate methodology to ensure accuracy of the results.

4 CONTRAINDICATIONS

KOVALTRY is contraindicated in patients who have a history of hypersensitivity reactions to the active substance, to any of the excipients, or to mouse or hamster proteins [see Description (11)].

5 WARNINGS AND PRECAUTIONS

5.1 Hypersensitivity Reactions

Hypersensitivity reactions, including anaphylaxis, are possible with KOVALTRY. Early signs of hypersensitivity reactions, which can progress to anaphylaxis, may include chest or throat tightness, dizziness, mild hypotension and nausea. Discontinue KOVALTRY if symptoms occur and seek immediate emergency treatment.

KOVALTRY may contain trace amounts of mouse and hamster proteins [see Description (11)]. Patients treated with this product may develop hypersensitivity to these non-human mammalian proteins.

5.2 Neutralizing Antibodies

Neutralizing antibody (inhibitor) formation has occurred following administration of KOVALTRY. Previously untreated patients (PUPs) are at greatest risk for inhibitor development with all Factor VIII products [see Adverse Reactions (6.1)]. Carefully monitor patients for the development of Factor VIII inhibitors, using appropriate clinical observations and laboratory tests. If expected plasma Factor VIII activity levels are not attained or if bleeding is not controlled as expected with administered dose, suspect the presence of an inhibitor (neutralizing antibody) [see Warnings and Precautions (5.5)].

5.3 Cardiovascular Risk Factors

Hemophilic patients with cardiovascular risk factors or diseases may be at the same risk to develop cardiovascular events as non-hemophilic patients when clotting has been normalized by treatment with Factor VIII.

5.4 Catheter-related Infections

Catheter-related infections may be observed when KOVALTRY is administered via central venous access devices (CVADs). These infections have not been associated with the product itself.

5.5 Monitoring Laboratory Tests

- Monitor plasma Factor VIII activity levels using a validated test to confirm that adequate Factor VIII levels have been achieved and maintained [see Dosage and Administration (2.1)].
- Monitor for development of Factor VIII inhibitors. Perform a Bethesda inhibitor assay if expected Factor VIII plasma levels are not attained or if bleeding is not controlled with the expected dose of KOVALTRY. Use Bethesda Units (BU) to report inhibitor titers.

6 ADVERSE REACTIONS

The most frequently reported adverse reactions in clinical trials (≥5%) were inhibitors in previously untreated patients (PUPs)/minimally treated patients (MTPs), pyrexia, headache, and rash (see Table 3).

6.1 Clinical Trials Experience

Because clinical trials are conducted under widely varying conditions, adverse reaction rates observed in the clinical trials of a drug cannot be directly compared to rates in clinical trials of another drug and may not reflect the rates observed in clinical practice.

The safety profile of KOVALTRY was evaluated in 236 (193 previously treated (PTPs), 43 PUPs/MTPs) patients, inclusive of 94 pediatric patients <12 years of age. The safety analysis was done using a pooled database from three multi-center, prospective, open-label clinical studies. The median time on clinical trial for the pooled safety population was 558 days with a median of 183 exposure days (EDs). The majority of patients (N=201) accumulated ≥ 100 EDs.

The total number of exposure days to KOVALTRY for all treatments including peri-operative management was 65029 EDs. Subjects who received KOVALTRY for perioperative management (N=5) with treatment period of 2 to 3 weeks and those who received single doses of KOVALTRY for PK studies (N=6) were excluded from the pooled safety analysis. Table 3 lists the adverse reactions reported during clinical studies. For PTPs, the frequency, type, and severity of adverse reactions in children are similar to those in adults.

Table 3: Adverse Reactions from pooled clinical studies (all age groups): Clinical trials 1, 2, and 3) (N=236)
MedDRA Primary System Organ Class Preferred term | Frequency of Adverse Drug Reactions N (%)
Blood and the Lymphatic System Disorders
Lymphadenopathy | 2 (0.8%)
Cardiac Disorders
Palpitation; Sinus tachycardia | 2 (0.8%); 2 (0.8%)
Gastrointestinal Disorders
Abdominal pain; Abdominal discomfort; Dyspepsia | 9 (3.8%); 3 (1.3%); 4 (1.7%)
General Disorders and Administration Site Conditions
Pyrexia; Chest discomfort; Injection site reactions [Includes injection site extravasation and hematoma, infusion site pain, pruritus, and swelling] | 22 (9.3%); 2 (0.8%); 6 (2.5%)
Immune System Disorders
Hypersensitivity | 1 (0.4%)
Nervous System Disorders
Dizziness; Dysgeusia; Headache | 3 (1.3%); 1 (0.4%); 20 (8.5%)
Psychiatric Disorders
Insomnia | 5 (2.1%)
Skin and Subcutaneous Tissue Disorders
Dermatitis allergic; Pruritus; Rash [Includes rash, rash erythematous, rash pruritic, and rash vesicular]; Urticaria | 2 (0.8%); 6 (2.5%); 13 (5.5%); 3 (1.3%)
Vascular disorders
Flushing | 1 (0.4%)

In PTPs (N=193), Factor VIII inhibitors occurred in 1 patient at a frequency of 0.5% (1/193) and in PUPs/MTPs (N=43) with a frequency of 54.8% (23/42); inhibitor analysis was based on 42 of 43 PUPs/MTPs, as one patient was unevaluable for inhibitor analysis and thus excluded.

Immunogenicity

All clinical trial subjects were monitored for neutralizing antibodies (inhibitors) to Factor VIII by the modified Bethesda assay using blood samples obtained prior to the first infusion of KOVALTRY, at defined intervals during the studies and at the completion visit.

Clinical trials with KOVALTRY evaluated a total of 204 treated pediatric and adult patients diagnosed with severe hemophilia A (Factor VIII <1%) with previous exposure to Factor VIII concentrates ≥50 EDs, no PTP developed neutralizing antibodies to Factor VIII. One case of transient low titer inhibitor (0.6 BU/mL (peak titer: 1.0 BU/mL)) occurred in a 13 year old PTP after 549 EDs concurrent with an acute infection and positive IgG anticardiolipin antibodies. The Factor VIII recovery was normal (2.7 IU/dL per IU/kg), annualized bleeding rate (ABR) was zero, and no change in therapy was required.

In the main phase of the clinical trial in PUPs/MTPs, Factor VIII inhibitors were detected in 23 of 42 patients (54.8%, 95% CI: 39 to 70%) with a median (range) of 9 (4-42) EDs at the time of the first positive inhibitor test. Of these, 6 (14.3%) patients had low titer inhibitors (≤ 5.0 BU) who continued on treatment and had negative inhibitor results at the end of the study. In 17 (40.5%) patients who developed high titer inhibitors (> 5.0 BU), high-risk mutations for inhibitor development were identified in 12 (85.7%) of 14 patients with available FVIII mutation data.

The detection of antibody formation is dependent on the sensitivity and specificity of the assay. Additionally, the observed incidence of antibody (including neutralizing antibody) positivity in an assay may be influenced by several factors including assay methodology, sample handling, timing of sample collection, concomitant medications, and underlying disease. For these reasons, it may be misleading to compare the incidence of antibodies to KOVALTRY with the incidence of antibodies to other products.

8 USE IN SPECIFIC POPULATIONS

8.1 Pregnancy

Risk Summary

There are no data with KOVALTRY use in pregnant women to inform on drug-associated risk. Animal reproduction studies have not been conducted using KOVALTRY. It is not known whether KOVALTRY can cause fetal harm when administered to a pregnant woman or can affect reproduction capacity. In the U.S. general population, the estimated background risk of major birth defects and miscarriage in clinically recognized pregnancies is 2-4% and 15-20%, respectively.

8.2 Lactation

Risk Summary

There is no information regarding the presence of KOVALTRY in human milk, the effects on the breastfed infant, or the effects on milk production. The developmental and health benefits of breastfeeding should be considered along with the mother’s clinical need for KOVALTRY and any potential adverse effects on the breastfed infant from KOVALTRY or from the underlying maternal condition.

8.4 Pediatric Use

Safety and efficacy studies with KOVALTRY have been performed in 51 pediatric PTPs ≤12 years of age and 43 pediatric PUPs/MTPs <6 years of age [see Clinical Studies (14)].

Body weight adjusted clearance of Factor VIII in children ≤12 years of age is higher than in adults and adolescents. Consider higher or more frequent dosing in children to account for this difference in clearance [see Clinical Pharmacology (12.3)].

8.5 Geriatric Use

Clinical studies with KOVALTRY did not include patients aged 65 and over to determine whether or not they respond differently from younger patients. However, clinical experience with other Factor VIII products has not identified differences between the elderly and younger patients. As with any patient receiving recombinant Factor VIII, dose selection for an elderly patient should be individualized.

11 DESCRIPTION

KOVALTRY, Antihemophilic Factor (Recombinant), is a sterile, non-pyrogenic, white to slightly yellow powder for reconstitution contained in a single-dose vial. The final product does not contain any preservative. The reconstituted product is indicated for intravenous administration. The product is available in 250 IU, 500 IU, 1000 IU, 2000 IU, or 3000 IU nominal potencies; however, for each dosage strength the actual, assayed Factor VIII potency is directly printed on each vial label. The container closure system consists of a 10 mL, Type I glass vial sealed with a bromobutyl grey stopper and an aluminum crimp seal with plastic flip-off cap plus vial adapter. The vial adapter was designed to connect with the sterile water for injection (sWFI), prefilled diluent syringe. KOVALTRY is formulated with the following excipients: 2.2% glycine, 1% sucrose, 30 mM sodium chloride, 2.5 mM calcium chloride, 20 mM histidine and 80 ppm polysorbate 80. The pH of the reconstituted product is 6.6 to 7.0. Intravenous administration of sucrose contained in KOVALTRY will not affect blood glucose level.

The active substance in KOVALTRY is the unmodified full length recombinant Factor VIII glycoprotein comprising the human derived amino acid sequence. Post-translational modifications are similar to those of endogenous Factor VIII including glycosylation sites and sulfation of tyrosine sites. Manufacturing and quality controls ensure that both galactose-alpha-1,3-galactose (alpha-Gal) and N-glycolyl neuraminic acid (NGNA) content are below the 1% limit of detection established for each analytical method.

KOVALTRY is produced by a genetically engineered Baby Hamster Kidney (BHK) cell line into which the human Factor VIII gene was introduced together with the human heat shock protein 70 (HSP 70) gene. HSP 70 is an intracellular protein that improves proper folding of the Factor VIII protein. While KOVALTRY and Kogenate FS have the same protein backbone, human- and animal-derived raw materials are not added to the cell culture, purification, or formulation processes for KOVALTRY. In the manufacturing process for KOVALTRY, recombinant Factor VIII is secreted into cell culture medium and is purified from process- and product-related impurities using a series of chromatography and filtration steps. The production process incorporates two dedicated viral clearance steps: (1) a detergent treatment step for inactivation and (2) a 20 nanometer filtration step for removal of viruses and potential protein aggregates.

12 CLINICAL PHARMACOLOGY

12.1 Mechanism of Action

KOVALTRY temporarily replaces the missing clotting Factor VIII that is needed for effective hemostasis.

12.2 Pharmacodynamics

Plasma clotting time as measured by the activated partial thromboplastin time (aPTT) is prolonged in patients with hemophilia A. Treatment with KOVALTRY normalizes the aPTT.

12.3 Pharmacokinetics

The pharmacokinetics (PK) of KOVALTRY were investigated in PTPs (0 to 61 years of age) with severe Hemophilia A following administration of 50 IU/kg of KOVALTRY. The PK parameters of KOVALTRY are presented in Table 4 (one-stage clotting assay) and Table 5 (chromogenic substrate assay). The PK of KOVALTRY were similar between single and repeat dosing (in 19 subjects following 6 to 12 months of prophylaxis).

Table 4: Pharmacokinetic Parameters [Arithmetic Mean ± SD] for KOVALTRY (50 IU/kg dose), One-Stage Clotting Assay
Parameter [unit] | 12 to 17 yrs (N=5) | ≥18 yrs (N=21)
AUC [IU*h/dL] | 1013.9 ± 286.8 | 1601.3 ± 520.0
Cmax [IU/dL] | 91.7 ± 28.7 | 99.7 ± 14.9
t½ [h] | 11.7 ± 1.11 | 14.3 ± 3.7
MRTIV [h] | 16.1 ± 0.8 | 19.8 ± 5.7
Vss [dL/kg] | 0.85 ± 0.24 | 0.63 ± 0.11
CL [dL/h/kg] | 0.053 ± 0.017 | 0.035 ± 0.012

AUC: area under the curve

Cmax: maximum drug concentration in plasma after single dose

t½ : terminal half-life

MRTIV: mean residence time after an IV administration

Vss: apparent volume distribution at steady-state

CL: clearance

The PK parameters of KOVALTRY for subjects across age groups are shown in Table 5. In general, children <12 years of age demonstrated lower plasma concentrations when compared to PTP children ≥12 years of age.

Table 5: Pharmacokinetic Parameters [Arithmetic Mean ± SD] for KOVALTRY (50 IU/kg dose), Chromogenic Substrate Assay
Parameter [unit] | 0 to <2 yrs; (N=4) | 2 to <6 yrs; (N=6) | 6 to <12 yrs (N=10)b | 12 to 17 yrs (N=5) | ≥18 yrs (N=21)
AUC [IU*h/dL] | 1232.5 ± 581.3 | 1484.8 ± 411.3a | 1214.5 ± 395.1 | 1572.0 ± 448.0 | 2103.4 ± 702.8
Cmax [IU/dL] | 96.1 ± 20.4 | 83.3 ± 28.7 | 81.6± 17.8 | 132.5 ± 46.3 | 133.1 ± 20.4
t½ [h] | 9.6 ± 3.1 | 12.2 ± 3.1a | 12.0 ± 2.1 | 14.4 ± 5.5 | 14.2 ± 3.5
MRTIV [h] | 14.1 ± 4.7 | 17.9 ± 4.1a | 17.8 ± 2.9 | 19.8 ± 5.8 | 19.9 ± 4.9
Vss [dL/kg] | 0.63 ± 0.18 | 0.60 ± 0.15a | 0.79 ± 0.23 | 0.71 ± 0.39 | 0.50 ± 0.11
CL [dL/h/kg] | 0.050 ± 0.024 | 0.034 ± 0.011a | 0.045 ± 0.016 | 0.034 ± 0.010 | 0.027 ± 0.010

a n=5
b One subject considered PK outlier was excluded

Incremental Recovery analysis after 6 months of prophylactic treatment yielded comparable results with incremental recovery after the first dose (see Table 6).

Table 6: Incremental Recovery in PTPs
 | 0 to <6 yrs N=25 | 6 to 12 yrs N=25 | ≥12 yrs N=115
Chromogenic substrate assay resultsa; Median (Q1; Q3); (IU/dL per IU/kg) | 1.6 (1.3; 1.9) | 1.7 (1.4; 2.0) | 2.3 (1.8; 2.6)
One-stage assay resultsa; Median (Q1; Q3); (IU/dL per IU/kg) | - | - | 2.2 (1.8; 2.4)

aStart of trial

13 NONCLINICAL TOXICOLOGY

13.1 Carcinogenesis, Mutagenesis, Impairment of Fertility

Long-term studies in animals to evaluate the carcinogenic potential of KOVALTRY or other studies to determine the effects of KOVALTRY on fertility have not been performed. KOVALTRY was negative in the modified in-vitro (Mammalian Mutation and Chromosome Aberration Assay with Mouse Lymphoma Cells) genotoxicity test. KOVALTRY is expected to have no mutagenic potential.

14 CLINICAL STUDIES

The safety and efficacy of KOVALTRY for on-demand treatment and control of bleeding episodes, perioperative management of bleeding, and routine prophylaxis in subjects with severe hemophilia A (<1% Factor VIII) was evaluated in three international (including U.S.) clinical studies. Immunocompetent subjects with severe hemophilia A (Factor VIII activity ≤1%) and no history of Factor VIII inhibitors were eligible for the trials.

Trial 1: a multi-center, open-label, cross-over, uncontrolled, study in adolescent and adult (age ≥12 years to <65 years) PTPs (≥150 EDs) evaluated the pharmacokinetics, efficacy and safety of routine prophylaxis, and perioperative management of bleeding of KOVALTRY (see Table 7). The primary efficacy variable was ABR. The prophylactic regimen was 20 to 50 IU/kg two or three times per week in which the dosing frequency was assigned by the investigator based on the subject’s individual requirements.

Trial 2: a multi-center, open-label, cross-over, uncontrolled, randomized study in adolescent and adult (age ≥12 years to <65 years) PTPs (≥150 EDs) evaluated the superiority of prophylaxis over on-demand treatment with KOVALTRY over a one-year treatment period (see Table 7). The primary efficacy variable was ABR. The prophylactic regimen was 20 to 30 IU/kg two times per week or 30 to 40 IU/kg three times per week and the treatment group was assigned by randomization.

Trial 3: a multi-center, open-label, uncontrolled study that evaluated the pharmacokinetics, efficacy and safety of routine prophylaxis, and perioperative management of bleeding of KOVALTRY (see Table 8) in previously treated patients (PTPs; ≥50 EDs) ≤12 years of age (Part A) and previously untreated patients (PUPs) and minimally treated patients (MTPs; ≤3 EDs) <6 years of age (Part B). The primary efficacy variable was annualized number of total bleeds during routine prophylaxis that occurred within 48 hours following previous prophylaxis infusion. ABR during prophylaxis, independent of time of infusion, was also analyzed. In Part A, the prophylactic regimen was 25 to 50 IU/kg at frequencies of either 2 times per week, 3 times per week or every other day and could be adapted to an individual subject’s need by the investigator.

In all studies, treatments of breakthrough bleeds and perioperative management were at the investigator’s discretion based on standard of care.

A total of 204 previously treated subjects (153 subjects ≥12 years of age and 51 subjects <12 years of age) and 43 PUPs/MTPs <6 years of age were treated in the clinical trials. Amongst the PTPs, 174 subjects were treated for at least 12 months and 78 of these subjects were treated for 24 months. Amongst the PUPs/MTPs, 34 subjects were treated for at least 12 months and 20 of these subjects were treated for 24 months.

Table 7: Overview of Trial 1 (Prophylaxis Treatment Phase) and Trial 2
 | Trial 1 (N=62) | Trial 2 (N=80)
Age: mean ± SD | 31.5 ± 12.7 years | 29.6 ± 11.0 years
Previous treatment: % | Prophylaxis: 80.6% | On-demand: 100%
Number of Target joints at baseline: mean ± SD | 1.4 ± 1.3 | 3.0 ± 2.1
Joint hemorrhage history (during 12 months prior to study): mean ± SD of joint bleeds | 8.0 ± 11.9 | 32.1 ± 23.8

Table 8: Overview of Trial 3
 | Trial 3
 | PTPs 0 to <6 yrs (N=25) | PTPs 6 to 12 yrs (N=26)
Age: mean ± SD (range) | 3.8 ± 1.3 years (1-5) | 8.8 ± 1.8 years (6-11)
Previous treatment: % | Prophylaxis: 92.0% | Prophylaxis: 65.4%
Number of Target joints at baseline: mean ± SD | 0.2 ± 0.4 | 0.7 ± 1.1

On-demand Treatment and Control of Bleeding Episodes

Adolescents and Adults

A total of 1892 bleeding episodes in 110 subjects were treated with KOVALTRY in Trial 1 and Trial 2 (see Table 9). The majority of the bleeding episodes were spontaneous, localized in joints, and mild to moderate in severity.

In Trial 1 and Trial 2, the treatment responses in a total of 1859 treated bleeds were assessed by the subjects compared to their previous treatment experience.

Table 9: On-demand Treatment and Control of Bleeding Episodes in Adolescents and Adults Treated with KOVALTRY
Characteristics of Bleeding Episodes | Trial 1 |  | Trial 2
Characteristics of Bleeding Episodes | Prophylaxis Main Study N=62 | Prophylaxis Extension N=55 | Prophylaxis N=59 | On-demand N=21
Total number of bleeds | 241 | 154 | 293 | 1204
Spontaneous: n/total (%) | 153/241 (63.5%) | 79/150 [Total number excluding uncharacterized bleeds] (52.7%) | 209/283 (73.9%) | 943/1202 (78.5%)
Trauma: n/total (%) | 79/241 (32.8%) | 70/150 (46.7%) | 74/283 (26.1%) | 258/1202 (21.5%)
Joint bleeds: n/total (%) | 191/241 (79.3%) | 120/154 (77.9%) | 255/293 (87.0%) | 924/1197 (77.2%)
Mild/moderate: n/total (%) | 215/241 (89.2%) | 130/153 (84.9%) | 260/293 (88.8%) | 1092/1196 (91.3%)
% of bleeds treated with ≤2 infusions | 87.0% |  | 96.2% | 95.3%
Response to treatment of bleeds assessed as “Excellent” or “Good”: n/total [The % is calculated from number of treated bleeds assessed for response] (%) | 190/235 (80.9%) | 107/149 (71.8%) | 172/279 (61.6%) | 834/1196 (69.7%)
Median dose per infusion (range) | 31.6 IU/kg (14-67 IU/kg) |  | 29.4 IU/kg (19-49 IU/kg) | 22.0 IU/kg (11-35 IU/kg)

Children 12 Years of Age and Younger

A total of 97 bleeding episodes in 28 previously treated pediatric subjects and 105 bleeding episodes in 37 PUPs/MTPs were treated with KOVALTRY. Majority (96.9% in PTPs and 97.1% in PUPs/MTPs) of the bleeds were mild to moderate in severity for both groups. Fifty-nine (72.8%) and 62 (59.0%) bleeds were trauma related for the previously treated subjects and PUPS/MTPs, respectively. During the 6 month treatment period, the median dose of KOVALTRY for the treatment of breakthrough bleeds in the previously treated subjects was 36.94 IU/kg per infusion (range 20.8–71.6 IU/kg).

Assessment of response to treatment of bleeds was as follows:

Excellent: Abrupt pain relief and/or improvement in signs of bleeding with no additional infusion administered; Good: Definite pain relief and/or improvement in signs of bleeding but possibly requiring more than one infusion for complete resolution; Moderate: Probable or slight improvement in signs of bleeding with at least one additional infusion for complete resolution; Poor: No improvement at all between infusions or condition worsens.

The hemostatic efficacy in on-demand treatment of bleeds was assessed as either “good” or “excellent” in 90.1% of cases (97.8% in the younger age group and 81.0% in the older age group). Majority of bleeds (89.7%) were successfully treated with ≤2 infusions. Response to treatment was similar for children aged 0 to <6 compared to 6 to 12 years of age (see Table 10).

Table 10: On-demand Treatment and Control of Bleeding Episodes in Children Treated with KOVALTRY
Characteristics of Bleeding Episodes | Trial 3
Characteristics of Bleeding Episodes | PTPs 0 to <6 yrs (N=25) | PTPs 6 to 12 yrs (N=26) | PTPs 0 to 12 yrs (N=51)
Total number of bleeds | 52 | 45 | 97
Spontaneous: n/total (%) | 8/44 [Total number of treated bleeds] (18.2%) | 12/37 (32.4%) | 20/81 (24.7%)
Trauma: n/total (%) | 36/44 (81.8%) | 23/37 (62.2%) | 59/81 (72.8%)
Joint bleeds: n/total (%) | 10/52 (19.2%) | 22/45 (48.9%) | 32/97 (33.0%)
Mild/moderate: n/total (%) | 50/52 (96.2%) | 44/45 (97.8%) | 94/97 (96.9%)
% of bleeds treated with ≤2 infusions | 92.4% | 86.7% | 89.7%
Response to treatment of bleeds assessed as “Excellent” or “Good”: n/total [The % is calculated from number of treated bleeds assessed for response] (%) | 43/44 (97.8%) | 30/37 (81.0%) | 73/81 (90.1%)
Median dose per infusion (range) | 38.7 IU/kg (20.8–71.6 IU/kg) | 32.4 IU/kg (21.7–50.0 IU/kg) | 36.9 IU/kg (20.8–71.6 IU/kg)

Perioperative Management

A total of 14 major and 46 minor surgeries were performed in 44 previously treated subjects (43 adults and adolescents and 1 child under 12 years of age) with severe hemophilia A. Seven of the 14 major surgeries in PTPs were orthopedic procedures, including joint replacement. Approximately 51% of the minor surgeries in PTPs were dental extractions. All subjects received KOVALTRY as bolus infusions. In the adolescent and adult subjects, the initial KOVALTRY doses administered ranged between 3000–5000 IU. The median total dose on the day of surgery was 107.5 IU/kg (range 60–207 IU/kg). In a single previously treated subject younger than 12 years of age who underwent a major surgery, the total initial KOVALTRY dose administered was 2500 IU (108.7 IU/kg).

The blood loss, during and after surgery, was within expected ranges. Hemostatic control was assessed by surgeons as “good” (perioperative bleeding slightly but not clinically significantly increased over expectations for the non-hemophilic patient; treatment similar to non-hemophilic patient) or “excellent” (perioperative blood loss similar to the non-hemophilic patient).

Routine Prophylaxis

Adolescents and Adults

A total of 140 subjects were treated with KOVALTRY for at least 12 months with median (range) 157 EDs (25-178) in Trial 1, [305 EDs (25-355) inclusive of extension phase], and 153 EDs (103-187) in Trial 2 (see Table 11). In both studies, subjects in the Intent-to-Treat (ITT) population received 95% to 100% of the prescribed number of prophylaxis infusions.

Table 11: Prophylaxis Treatment with KOVALTRY in Adolescents and Adults – Treatment Exposure
 | Trial 1 (N=62) [Trial 1 included PK, safety and efficacy of prophylaxis and hemostasis during surgeries. Prophylaxis phase data are presented.] | Trial 2 (N=59)
Median nominal prophylaxis dose/ infusion (range); All; Prophylaxis 2 times per week; Prophylaxis 3 times per week | 31.2 IU/kg (21-43 IU/kg); 35.0 IU/kg (21-42 IU/kg); 31.1 IU/kg (24-43 IU/kg) | 31.7 IU/kg (21-42 IU/kg); 30.4 IU/kg (21-34 IU/kg); 37.4 IU/kg (30-42 IU/kg)
Treatment duration | 1 year main study | 1 year
Trial 1: 2 times per week (n=18); 3 times per week (n=44)
Trial 2: 2 times per week (n=28); 3 times per week (n=31)

The mean and median ABR for the ITT population in Trial 1 was 3.8 ± 5.2 and 1 bleed/year, respectively. In Trial 2, comparison of the bleeding rates between subjects receiving on-demand therapy versus prophylaxis in an ANOVA demonstrated a statistically significant difference (p<0.0001) in the median ABR in subjects receiving on-demand therapy (60 bleeds per year) as compared to subjects receiving prophylaxis (2 bleeds per year). In Trial 2, mean ABR in subjects receiving on-demand therapy was 57.7 ± 24.6 versus 4.9 ± 6.8 in the subjects receiving prophylaxis.

Table 12: ABR in Adolescent and Adult Subjects
 | Trial 1 (N=62) |  | Trial 2 (N=59)
 | 2 times per week (n=18) | 3 times per week (n=44) | 2 times per week (n=28) | 3 times per week (n=31)
ABR Median (IQR [IQR = Interquartile Range] Q1; Q3)
All Bleeds | 1.0 (0.0; 8.0) | 2.0 (0.5; 5.0) | 4.0 (0.0; 8.0) Month 1-6 [Month 1-6 refers to the first six months of the treatment period and Month 7-12 refer to the second six months of the treatment period] : 4.1; Month 7-12: 1.1 | 2.0 (0.0; 4.9) Month 1-6: 2.0; Month 7-12: 2.0
Spontaneous Bleeds | 0.5 (0.0; 2.0) | 1.0 (0.0; 3.9) | 2.0 (0.0; 6.5) | 0.0 (0.0; 3.0)
Joint Bleeds | 0.5 (0.0; 7.0) | 1.8 (0.0; 3.0) | 2.5 (0.0; 7.5) | 1.0 (0.0; 4.0)
Subjects with Zero Bleeding Episodes [Observation of one-year treatment period] % (n) | 37.5% (6/16 [n=total number of subjects with zero bleeds]) | 62.5% (10/16) | 28.6% (8/28 [n=total number of subjects randomized to treatment arms]) | 25.8% (8/31)

The ABR for subjects (n=21) receiving on-demand therapy in Trial 2 [median (IQR Q1; Q3)] for all bleeds: 60 (41.7; 76.3); spontaneous bleeds: 42.1 (24.3; 61.3); joint bleeds: 38.8 (24.3; 60.0).

Children 12 Years of Age and Younger

In Part A, a total of 51 PTPs were treated with KOVALTRY for at least 6 months with median (range) 73 EDs (37-103) (see Table 13). Subjects received >95% of the prescribed number of prophylaxis infusions.

Table 13: Prophylaxis Treatment with KOVALTRY in Children 12 Years of Age or Younger – Treatment Exposure
 | Trial 3
 | PTPs 0 to <6 yrs (N=25) | PTPs 6 to 12 yrs (N=26)
Treatment regimen [Treatment regimen at the start of the study. Study duration was six months.] during study (6 months) n (%); 2 times per week; 3 times per week or every other day | 9 (36%); 16 (64%) | 13 (50%); 13 (50%)
Nominal prophylaxis dose per infusion, median (range) | 36.4 IU/kg (21-58 IU/kg) | 31.8 IU/kg (22-50 IU/kg)

In children 12 years of age and younger (n=51), the median (IQR Q1; Q3) ABR within 48 hours after prophylactic infusion was 0 (0; 4) for all bleeds, and 0 (0; 0) for spontaneous and joint bleeds. The median (IQR Q1; Q3) ABR during prophylactic treatment independent of time of infusion was 1.9 (0; 6) for all bleeds, 0 (0; 0) for spontaneous bleeds and 0 (0; 2) for joint bleeds. The mean ABR within 48 hours after prophylactic infusion was 2.04 ± 2.91. The mean ABR at any time during the prophylaxis regimen was 3.75 ± 4.98.

In both age groups (0 to <6 years and 6 to 12 years), the ABR for spontaneous bleeds and joint bleeds within 48 hours after prophylactic treatment [ABR median (IQR Q1; Q3)] was 0 (0; 0). The median (IQR Q1; Q3) annualized number of spontaneous bleeds during prophylactic treatment independent of time of infusion was 0 (0; 0). The median (IQR Q1; Q3) annualized number of joint bleeds during prophylactic treatment independent of time of infusion was 0 (0; 1.9) in 0 to <6 years age group and 0 (0; 2.1) in 6 to 12 years age group (see Table 14).

The majority (32/53) of bleeds that occurred within 48 hours after a previous prophylaxis infusion were trauma related. Twenty-three (45.1%) subjects reported no bleeds during the six-month prophylaxis period.

Table 14: ABR in Children 12 Years of Age or Younger
 | Trial 3
 | PTPs 0 to <6 yrs (N=25) |  | PTPs 6 to 12 yrs (N=26)
 | Within 48 hrs after prophylactic treatment | During prophylactic treatment [Independent of time of infusion] | Within 48 hrs after prophylactic treatment | During prophylactic treatment
All Bleeds ABR Median (IQR [IQR = Interquartile Range] Q1; Q3) | 1.9 (0.0; 4.0) | 2.0 (0.0; 6.0) | 0.0 (0.0; 2.0) | 0.9 (0.0; 5.8)
Number of Subjects with Zero Bleeding Episodes (%) | 10 (40%) |  | 13 (50%)

16 HOW SUPPLIED/STORAGE AND HANDLING

How Supplied

KOVALTRY is available as a lyophilized powder in single-dose glass vials, one vial per carton. It is supplied with a sterile vial adapter with 15-micrometer filter and a prefilled diluent glass barrel syringe, which together serve as a needleless reconstitution system. The prefilled diluent syringe contains Sterile Water for Injection, USP. An administration set is also provided in the package. Available sizes:

Nominal Strength (IU) | Diluent (mL) | Kit NDC Number | Color Code
250 | 2.5 | 0026-3821-25 | Blue
500 | 2.5 | 0026-3822-25 | Green
1000 | 2.5 | 0026-3824-25 | Red
2000 | 5.0 | 0026-3826-50 | Yellow
3000 | 5.0 | 0026-3828-50 | Gray

Actual Factor VIII activity in IU is stated on the label of each KOVALTRY vial.

The product vial and diluent syringe are not made with natural rubber latex.

Storage and Handling

Product as Packaged for Sale

- Store KOVALTRY at +2°C to +8°C (36°F to 46°F) for up to 30 months from the date of manufacture. Do not freeze. Within this period, KOVALTRY may be stored for a single period of up to 12 months at temperatures up to +25°C or 77°F.
- Record the starting date of room temperature storage on the unopened product carton. Once stored at room temperature, do not return the product to the refrigerator. The shelf-life then expires after storage at room temperature for 12 months, or after the expiration date on the product vial, whichever is earlier.
- Do not use KOVALTRY after the expiration date indicated on the vial.
- Protect KOVALTRY from extreme exposure to light and store the vial with the lyophilized powder in the carton prior to use.

Product After Reconstitution

- Administer reconstituted KOVALTRY as soon as possible. If not, store at room temperature for no longer than 3 hours.
- Do not use KOVALTRY if the reconstituted solution is cloudy or has particulate matter.
- Use the administration set provided.

17 PATIENT COUNSELING INFORMATION

- Advise the patient to read the FDA-approved patient labeling (Patient Information and Instructions for Use).
- Hypersensitivity reactions are possible with KOVALTRY [see Warnings and Precautions (5.1)]. Warn patients of the early signs of hypersensitivity reactions (including tightness of the chest or throat, dizziness, mild hypotension and nausea during infusion) which can progress to anaphylaxis. Advise patients to discontinue use of the product if these symptoms occur and seek immediate emergency treatment with resuscitative measures such as the administration of epinephrine and oxygen.
- Inhibitor formation may occur at any time in the treatment of a patient with hemophilia A [see Warnings and Precautions (5.2)]. Advise patients to contact their physician or treatment center for further treatment and/or assessment, if they experience a lack of clinical response to Factor VIII replacement therapy, as this may be a manifestation of an inhibitor.

FDA-Approved Patient Labeling

Patient Information

KOVALTRY (KOH-vahl-tree)

Antihemophilic Factor (Recombinant)

This leaflet summarizes important information about KOVALTRY with vial adapter. Please read it carefully before using this medicine. This information does not take the place of talking with your healthcare provider, and it does not include all of the important information about KOVALTRY. If you have any questions after reading this, ask your healthcare provider.

Do not attempt to self-infuse unless you have been taught how by your healthcare provider or hemophilia center.

What is KOVALTRY?

KOVALTRY is a medicine used to replace clotting factor (Factor VIII or antihemophilic factor) that is missing in people with hemophilia A (also called “classic” hemophilia). Hemophilia A is an inherited bleeding disorder that prevents blood from clotting normally.

KOVALTRY is used to treat and control bleeding in adults and children with hemophilia A. Your healthcare provider may give you KOVALTRY when you have surgery. KOVALTRY can reduce the number of bleeding episodes in adults and children with hemophilia A when used regularly (prophylaxis).

KOVALTRY is not used to treat von Willebrand Disease.

Who should not use KOVALTRY?

You should not use KOVALTRY if you

- are allergic to rodents (like mice and hamsters).
- are allergic to any ingredients in KOVALTRY.

What should I tell my healthcare provider before I use KOVALTRY?

- Tell your healthcare provider about all of your medical conditions.
- Tell your healthcare provider and pharmacist about all of the medicines you take, including all prescription and non-prescription medicines, such as over-the-counter medicines, supplements, or herbal remedies.
- Tell your healthcare provider if you have been told you have heart disease or are at risk for heart disease.
- Tell your healthcare provider if you have been told that you have inhibitors to Factor VIII (because KOVALTRY may not work for you).

What are the possible side effects of KOVALTRY?

The common side effects of KOVALTRY are fever, headache, and rash, in addition to inhibitors in patients who were not previously treated or minimally treated with Factor VIII products.

Your body may make antibodies, called “inhibitors” against KOVALTRY, which may stop KOVALTRY from working properly. If your bleeding is not adequately controlled, it could be due to the development of Factor VIII inhibitors. Consult with your healthcare provider to make sure you are carefully monitored with blood tests for the development of inhibitors to Factor VIII.

Allergic reactions may occur with KOVALTRY. Call your healthcare provider right away and stop treatment if you get tightness of the chest or throat, dizziness, decrease in blood pressure, and nausea.

These are not all the possible side effects with KOVALTRY. You can ask your healthcare provider for information that is written for healthcare professionals.

Tell your healthcare provider about any side effect that bothers you or that does not go away.

What are the KOVALTRY dosage strengths?

KOVALTRY with 2.5 mL or 5 mL Sterile Water for Injection (SWFI) comes in five different dosage strengths labeled as International Units (IU): 250 IU, 500 IU, 1000 IU, 2000 IU, and 3000 IU. The five different strengths are color-coded as follows:

Blue | 250 IU with 2.5 mL SWFI
Green | 500 IU with 2.5 mL SWFI
Red | 1000 IU with 2.5 mL SWFI
Yellow | 2000 IU with 5 mL SWFI
Gray | 3000 IU with 5 mL SWFI

How do I store KOVALTRY?

Do not freeze KOVALTRY.

Store KOVALTRY at +2°C to +8°C (36°F to 46°F) for up to 30 months from the date of manufacture. Within this period, KOVALTRY may be stored for a period of up to 12 months at temperatures up to +25°C or 77°F.

Record the starting date of room temperature storage clearly on the unopened product carton. Once stored at room temperature, do not return the product to the refrigerator. The product then expires after storage at room temperature for 12 months, or after the expiration date on the product vial, whichever is earlier. Store vials in their original carton and protect them from extreme exposure to light.

Administer reconstituted KOVALTRY as soon as possible. If not, store at room temperature for no longer than 3 hours.

Throw away any unused KOVALTRY after the expiration date.

Do not use reconstituted KOVALTRY if it is not clear.

What else should I know about KOVALTRY and hemophilia A?

Finding veins for injections may be difficult in young children. When frequent injections are required, your healthcare provider may propose to have a device surgically placed under the skin to facilitate access to the bloodstream. These devices may result in infections.

Medicines are sometimes prescribed for purposes other than those listed here. Do not use KOVALTRY for a condition for which it is not prescribed. Do not share KOVALTRY with other people, even if they have the same symptoms that you have.

This leaflet summarizes the most important information about KOVALTRY. If you would like more information, talk to your healthcare provider. You can ask your healthcare provider or pharmacist for information about KOVALTRY that was written for healthcare professionals.

Instructions for Use

KOVALTRY (KOH-vahl-tree)

Antihemophilic Factor (Recombinant)

Do not attempt to self-infuse unless you have been taught how by your healthcare provider or hemophilia center.

You should always follow the specific instructions given by your healthcare provider. The steps listed below are general guidelines for using KOVALTRY. If you are unsure of the procedures, please call your healthcare provider before using.

Call your healthcare provider right away if bleeding is not controlled after using KOVALTRY.

Your healthcare provider will prescribe the dose that you should take.

Your healthcare provider may need to take blood tests from time to time.

Talk to your healthcare provider before traveling. You should plan to bring enough KOVALTRY for your treatment during this time.

See the step-by-step instructions below for reconstituting KOVALTRY with vial adapter. Follow the specific infusion instruction leaflet included with the infusion set provided.

Carefully handle KOVALTRY. Dispose of all materials, including any leftover reconstituted KOVALTRY product, in an appropriate container.

Reconstitution

Always work on a clean surface and wash your hands before performing the following procedure. Use only the components for reconstitution and administration that are provided with each package of KOVALTRY. If a package is opened or damaged, do not use this component. If these components cannot be used, please contact your healthcare provider.

Prepare a clean flat surface and gather all the materials needed for the infusion.

1. Warm the unopened diluent syringe and the concentrate vial to a temperature not to exceed 37°C or 99°F.

2. Remove protective cap from the vial (A). Aseptically cleanse the rubber stopper with a sterile alcohol swab, being careful not to handle the rubber stopper.

3. Place product vial on a firm, non-skid surface. Peel off the paper cover on the vial adapter plastic housing. Do not remove the adapter from the plastic housing. Holding the adapter housing, place over the product vial and firmly press down (B). The adapter will snap over the vial cap. Do not remove the adapter housing at this step.

4. Holding the syringe by the barrel, snap the syringe cap off the tip (C). Do not touch the syringe tip with your hand or any surface. Set the syringe aside for further use.

5. Now remove and discard the adapter plastic housing (D).

6. Attach the prefilled syringe to the vial adapter thread by turning clockwise (E).

7. Remove the clear plastic plunger rod from the carton. Grasp the plunger rod by the top plate. Avoid touching the sides and threads of the plunger rod. Attach the plunger rod by turning it clockwise into the threaded rubber stopper of the prefilled syringe (F).

8. Inject the diluent slowly by pushing down on the plunger rod (G).

9. Swirl vial gently until all powder on all sides of the vial is dissolved (H). Do not shake vial. Be sure that all powder is completely dissolved. Do not use if solution contains visible particles or is cloudy.

10. Push down on the plunger to push all air back into the vial. Then while holding the plunger down, turn the vial with syringe upside-down (invert) so the vial is now above the syringe (I).

11. Withdraw all the solution into the syringe by pulling the plunger rod back slowly and smoothly (J). Tilt the vial to the side and back to make sure all the solution has been drawn toward the large opening in the rubber stopper and into the syringe. Remove as much air as possible before removing the syringe from the vial by slowly and carefully pushing the air back into the vial.

12. Detach the syringe with plunger rod from the vial adapter by turning counter-clockwise. Attach the syringe to the administration set provided and inject intravenously (K). NOTE: follow instructions for infusion set provided.

Pooling

If the dose requires more than one vial, reconstitute each vial as described above with the diluent syringe provided. To combine the content of the vials, use a larger plastic syringe (not provided) to pool the solution into the syringe and administer as usual.

Rate of Administration

The entire dose of KOVALTRY can usually be infused within 1 to 15 minutes. Your healthcare provider will determine the rate of administration that is best for you.

Resources at Bayer available to the patient:

For Adverse Reaction Reporting, contact Bayer Medical Communications 1-888-84-BAYER (1-888-842-2937)

To receive more product information, contact KOVALTRY Customer Service 1-888-606-3780

Bayer Reimbursement HELPline 1-800-288-8374

For more information, visit www.KOVALTRY-us.com

Bayer HealthCare LLC
Whippany, NJ 07981 USA

U.S. License No. 8

This Patient Information and Instructions for Use have been approved by the U.S. Food and Drug Administration. Revised: 10/2021

PACKAGE LABEL

NDC 0026-3821-25
Kovaltry 250 IU Range
Antihemophilic Factor (Recombinant)
Recombinant Factor VIII

with Vial Adapter

For Intravenous Use Only

Needleless Reconstitution Set

PACKAGE LABEL

NDC 0026-3822-25
Kovaltry 500 IU Range
Antihemophilic Factor (Recombinant)
Recombinant Factor VIII

with Vial Adapter

For Intravenous Use Only

Needleless Reconstitution Set

PACKAGE LABEL

NDC 0026-3824-25
Kovaltry 1000 IU Range
Antihemophilic Factor (Recombinant)
Recombinant Factor VIII

with Vial Adapter

For Intravenous Use Only

Needleless Reconstitution Set

PACKAGE LABEL

NDC 0026-3826-50
Kovaltry 2000 IU Range
Antihemophilic Factor (Recombinant)
Recombinant Factor VIII

with Vial Adapter

For Intravenous Use Only

Needleless Reconstitution Set

PACKAGE LABEL

NDC 0026-3828-50
Kovaltry 3000 IU Range
Antihemophilic Factor (Recombinant)
Recombinant Factor VIII

with Vial Adapter

For Intravenous Use Only

Needleless Reconstitution Set